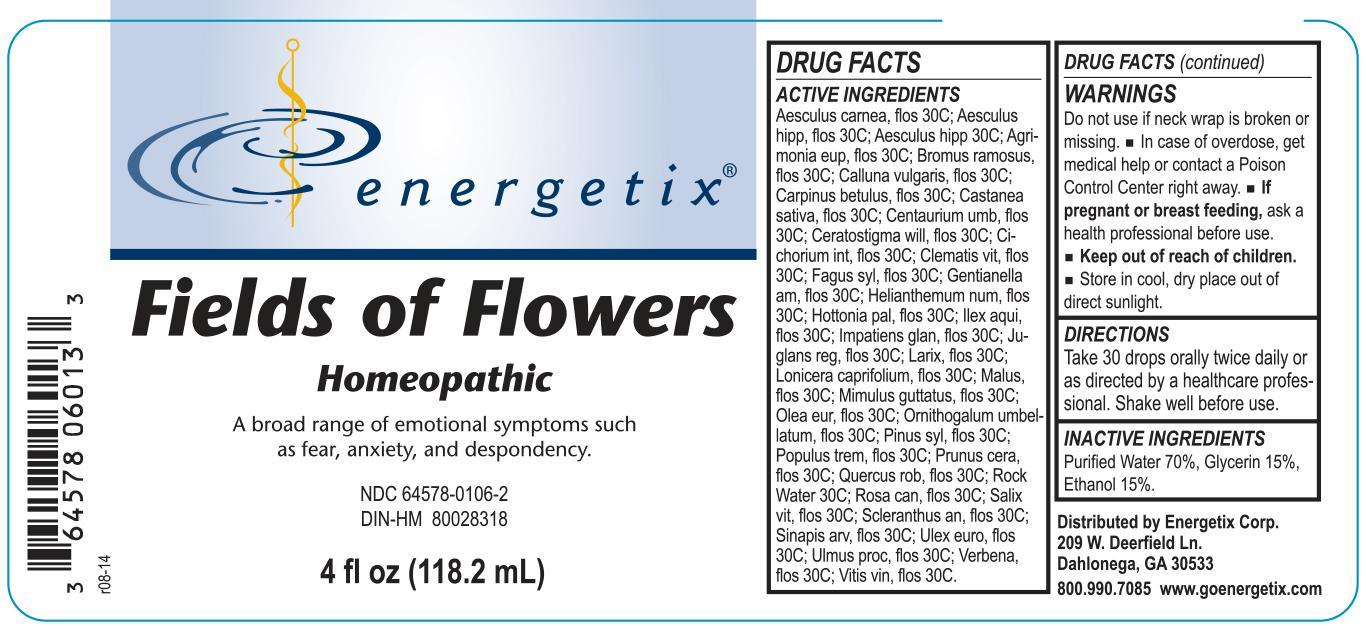 DRUG LABEL: Fields of Flowers
NDC: 64578-0106 | Form: LIQUID
Manufacturer: Energetix Corp
Category: homeopathic | Type: HUMAN OTC DRUG LABEL
Date: 20140825

ACTIVE INGREDIENTS: AESCULUS CARNEA FLOWER 30 [hp_C]/118.2 mL; AESCULUS HIPPOCASTANUM FLOWER 30 [hp_C]/118.2 mL; HORSE CHESTNUT 30 [hp_C]/118.2 mL; AGRIMONIA EUPATORIA FLOWER 30 [hp_C]/118.2 mL; BROMUS RAMOSUS FLOWER 30 [hp_C]/118.2 mL; CALLUNA VULGARIS FLOWERING TOP 30 [hp_C]/118.2 mL; CARPINUS BETULUS FLOWERING TOP 30 [hp_C]/118.2 mL; CASTANEA SATIVA FLOWER 30 [hp_C]/118.2 mL; CENTAURIUM ERYTHRAEA FLOWER 30 [hp_C]/118.2 mL; CERATOSTIGMA WILLMOTTIANUM FLOWER 30 [hp_C]/118.2 mL; CICHORIUM INTYBUS FLOWER 30 [hp_C]/118.2 mL; FAGUS SYLVATICA FLOWERING TOP 30 [hp_C]/118.2 mL; GENTIANELLA AMARELLA FLOWER 30 [hp_C]/118.2 mL; HELIANTHEMUM NUMMULARIUM FLOWER 30 [hp_C]/118.2 mL; HOTTONIA PALUSTRIS FLOWER 30 [hp_C]/118.2 mL; ILEX AQUIFOLIUM FLOWERING TOP 30 [hp_C]/118.2 mL; IMPATIENS GLANDULIFERA FLOWER 30 [hp_C]/118.2 mL; JUGLANS REGIA FLOWERING TOP 30 [hp_C]/118.2 mL; LARIX DECIDUA FLOWERING TOP 30 [hp_C]/118.2 mL; LONICERA CAPRIFOLIUM FLOWERING TOP 30 [hp_C]/118.2 mL; MALUS DOMESTICA FLOWER 30 [hp_C]/118.2 mL; MIMULUS GUTTATUS FLOWERING TOP 30 [hp_C]/118.2 mL; OLEA EUROPAEA FLOWER 30 [hp_C]/118.2 mL; ORNITHOGALUM UMBELLATUM FLOWERING TOP 30 [hp_C]/118.2 mL; PINUS SYLVESTRIS FLOWERING TOP 30 [hp_C]/118.2 mL; PRUNUS CERASIFERA FLOWER 30 [hp_C]/118.2 mL; QUERCUS ROBUR FLOWER 30 [hp_C]/118.2 mL; ROSA CANINA FLOWER 30 [hp_C]/118.2 mL; SALIX ALBA FLOWERING TOP 30 [hp_C]/118.2 mL; SCLERANTHUS ANNUUS FLOWERING TOP 30 [hp_C]/118.2 mL; SINAPIS ARVENSIS FLOWERING/FRUITING TOP 30 [hp_C]/118.2 mL; ULEX EUROPAEUS FLOWER 30 [hp_C]/118.2 mL; VERBENA OFFICINALIS FLOWERING TOP 30 [hp_C]/118.2 mL; VITIS VINIFERA FLOWERING TOP 30 [hp_C]/118.2 mL
INACTIVE INGREDIENTS: WATER 82.73 mL/118.2 mL; glycerin 17.72 mL/118.2 mL; ALCOHOL 17.72 mL/118.2 mL

Fields of Flowers

ACTIVE INGREDIENT

Aesculus carnea, flos 30C; Aesculus hipp, flos 30C; Aesculus hipp 30C; Agrimonia eup, flos 30C; Bromus ramosus, flos 30C; Calluna vulgaris, flos 30C; Carpinus betulus, flos 30C; Castanea sativa, flos 30C; Centaurium umb, flos 30C; Ceratostigma will, flos 30C; Cichorium int, flos 30C; Clematis vit, flos 30C; Fagus syl, flos 30C; Gentianella am, flos 30C; Helianthemum num, flos 30C; Hottonia pal, flos 30C; Ilex aqui, flos 30C; Impatiens glan, flos 30C; Juglans reg, flos 30C; Larix, flos 30C; Lonicera caprifolium, flos 30C; Malus, flos 30C; Mimulus guttatus, flos 30C; Olea eur, flos 30C; Ornithogalum umbellatum, flos 30C; Pinus syl, flos 30C; Populus trem, flos 30C; Prunus cera, flos 30C; Quercus rob, flos 30C; Rock Water 30C; Rosa can, flos 30C; Salix vit, flos 30C; Scleranthus an, flos 30C; Sinapis arv, flos 30C; Ulex euro, flos 30C; Ulmus proc, flos 30C; Verbena, flos 30C; Vitis vin, flos 30C.

Do not use if neck wrap is broken or missing.

OVERDOSAGE

In case of overdose, get medical help or contact a Poison Control Center right away.

PREGNANCY OR BREAST FEEDING

If pregnant or breast feeding, ask a health professional before use.

Keep out of reach of children.

STORAGE AND HANDLING

Store in cool, dry place out of direct sunlight.

QUESTIONS

800.990.7085 www.goenergetix.com

PURPOSE

A broad range of emotional symptoms such as fear, anxiety, and despondency.

INACTIVE INGREDIENT

Purified Water 70%, Glycerin 15%, Ethanol 15%.

DOSAGE AND ADMINISTRATION

Take 30 drops orally twice daily or as directed by a healthcare professional. Shake well before use.

INDICATIONS AND USAGE

A broad range of emotional symptoms such as fear, anxiety, and despondency.